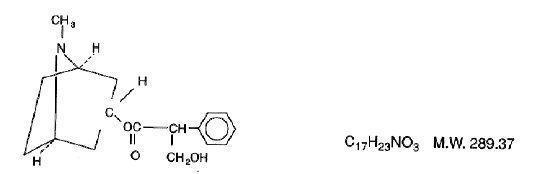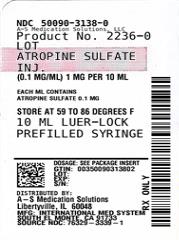 DRUG LABEL: 
                  Atropine Sulfate
                
NDC: 50090-3138 | Form: INJECTION
Manufacturer: A-S Medication Solutions
Category: prescription | Type: HUMAN PRESCRIPTION DRUG LABEL
Date: 20210326

ACTIVE INGREDIENTS: ATROPINE SULFATE 0.1 mg/1 mL

ATROPINE SULFATE
INJECTION, USP

DESCRIPTION

Atropine is chemically 1 α H, 5 α H - Tropan-3 α-ol (±) -tropate (ester), with the following structural formula:

Atropine rarely occurs as such in any of the plants and has been prepared by synthesis. It is usually employed in the form of atropine sulfate (the sulfate [2:1] monohydrate salt of atropine), which has much greater solubility in water.

Atropine Sulfate Injection, USP, is a sterile aqueous solution of atropine sulfate. Each mL contains atropine sulfate, 0.1 mg; sodium chloride, 8.8 mg, for isotonicity; citric acid, 0.63 mg, and sodium citrate, 0.29 mg, as buffers. May contain additional citric acid and/or sodium citrate for pH adjustment (3.0-6.5). The air above the liquid in the container has been displaced by nitrogen gas.

CLlNICAL PHARMACOLOGY

Atropine inhibits the muscarinic actions of acetylcholine at postganglionic parasympathetic neuroeffector sites including smooth muscle, secretory glands and CNS sites. Large doses may block nicotinic receptors at the autonomic ganglia and at the neuromuscular junction.

Specific anticholinergic responses are dose-related. Small doses of atropine inhibit salivary and bronchial secretions and sweating; moderate doses dilate the pupil, inhibit accommodation and increase the heart rate (vagolytic effect); larger doses will decrease motility of the GI and urinary tracts; very large doses will inhibit gastric acid secretion.

INDICATIONS AND USAGE

Atropine Sulfate Injection, USP, may be given parenterally as a pre-anesthetic medication in surgical patients to reduce salivation and bronchial secretions. It may also be used to suppress vagal activity associated with the use of halogenated hydrocarbons during inhalation anesthesia and reflex excitation arising from mechanical stimulation during surgery.

The antispasmodic action of atropine is useful in pylorospasm and other spastic conditions of the gastrointestinal tract. For ureteral and biliary colic, atropine concomitantly with morphine may be indicated.

Atropine relaxes the upper GI tract and colon during hypotonic radiography.

In poisoning by the organic phosphate cholinesterase inhibitors found in certain insecticides and by chemical warfare nerve gases, large doses of atropine relieve the muscarine-like symptoms and some of the central nervous system manifestations. It is also used as an antidote for mushroom poisoning due to muscarine in certain species such as Amanita muscaria.

CONTRAINDICATIONS

Atropine Sulfate is contraindicated in patients with a history of hypersensitivity to this drug.

Ocular: Narrow-angle glaucoma; adhesions (synechiae) between the iris and lens of the eye.
Cardiovascular: Tachycardia; unstable cardiovascular status in acute hemorrhage.
GI: Obstructive disease (e.g., achalasia, pyloroduodenal stenosis, or pyloric obstruction, cardiospasm, etc.); paralytic ileus; intestinal atony of the elderly or debilitated patient; severe ulcerative colitis; toxic megacolon complicating ulcerative colitis; hepatic disease.
GU: Obstructive uropathy (e.g., bladder neck obstruction due to prostatic hypertrophy); renal disease.
Musculoskeletal: Myasthenia gravis.

WARNINGS

Heat prostration can occur with anticholinergic drug use (fever and heat stroke due to decreased sweating) in the presence of a high environmental temperature.

Diarrhea may be an early symptom of incomplete intestinal obstruction, especially in patients with ileostomy or colostomy. Treatment of diarrhea with these drugs is inappropriate and possibly harmful.

Usage in the elderly: Elderly patients may react with excitement, agitation, drowsiness and other untoward manifestations to even small doses of anticholinergic drugs.

Usage in gastric ulcer may produce a delay in gastric emptying time and may complicate such therapy (antral stasis).

PRECAUTIONS

General:

Potentially hazardous tasks: Atropine may produce drowsiness, dizziness or blurred vision; patients should observe caution while driving or performing other tasks requiring alertness.

Atropine should be used with caution in:
CNS: Autonomic neuropathy.
Ocular: Glaucoma, light irides. If there is mydriasis and photophobia, dark glasses should be worn. Atropine should be used with caution in patients over 40 years of age because of the increased incidence of glaucoma.
GI: Hepatic disease; early evidence of ileus, as in peritonitis; ulcerative colitis (large doses may suppress intestinal motility and precipitate or aggravate toxic megacolon); hiatal hernia associated with reflux esophagitis (anticholinergics may aggravate it).
GU: Renal disease; prostatic hypertrophy. Patients with prostatism can have dysuria may require catheterization.
Endocrine: Hyperthyroidism.
Cardiovascular: Coronary heart disease; congestive heart failure; cardiac arrhythmias; tachycardia; hypertension.
Usage in biliary tract disease: The use of atropine should not be relied upon in the presence of complication of biliary tract disease.
Special risk patients: Atropine should be used cautiously in infants, small children and persons with Down’s syndrome, brain damage or spasticity.
Pulmonary: Debilitated patients with chronic lung disease; reduction in bronchial secretions can lead to inspissation and formation of bronchial plugs.

Atropine should be used cautiously in patients with asthma or allergies.

Drug Interactions:

Antihistamines, antipsychotics, antiparkinson drugs, alphaprodine, buclizine, meperidine, orphenadrine, benzodiazepines and tricyclic antidepressants may enhance the anticholinergic effects of atropine and its derivatives. Nitrates, nitrites, alkalinizing agents, primidone, thioxanthenes, methylphenidate, disopyramide, procainamide and quinidine may also potentiate side effects. Monoamine oxidase inhibitors block detoxification of atropine, and thus, potentiate its actions. Concurrent long-term therapy with corticosteroids or haloperidol may increase intraocular pressure. Atropine may antagonize the miotic actions of cholinesterase inhibitors.

The bronchial relaxation produced by sympathomimetics is enhanced by atropine.

Inhibition of gastric acid secretion by atropine is antagonized by guanethidine, histamine and reserpine.

Because of the potential for adverse effects, atropine should be used cautiously with digitalis, slow release digoxin tablets, cholinergics and neostigmine.

The I.V. administration of atropine in the presence of cyclopropane anesthesia can result in ventricular arrhythmias.

Atropine may enhance nitrofurantoin and thiazide-diuretic bioavailability by slowing GI motility.

The effects of metoclopramide on GI motility are antagonized by atropine.

Usage in Pregnancy:

Teratogenic Effect - Pregnancy Category B

Reproduction studies performed in mice at doses of 50 mg per kg of body weight have revealed no evidence of impaired fertility or harm to the fetus due to atropine. There are, however, no adequate and well-controlled studies in pregnant women. Because animal reproduction studies are not always predictive of human response, this drug should be used during pregnancy only if clearly needed.

Usage in Lactation:

Atropine may be excreted in milk, causing infant toxicity, and may reduce breast milk production. Documentation is lacking or conflicting. Safety for use in nursing mothers has not been established.

Usage in Children:

(See DOSAGE AND ADMINISTRATION recommendations under “Usual Pediatric Dosage”).

ADVERSE REACTIONS

GI: Xerostomia; altered taste perception; nausea; vomiting; dysphagia; heartburn, constipation; bloated feeling; paralytic ileus; gastroesophageal reflux.
GU: Urinary hesitancy and retention; impotence.
Ocular: Blurred vision; mydriasis; photophobia; cycloplegia; increased intraocular pressure.
Cardiovascular: Palpitations; bradycardia (following low doses of atropine); tachycardia (after higher doses).
CNS: Headache; flushing; nervousness; drowsiness; weakness; dizziness; insomnia; fever. Elderly patients may exhibit mental confusion or excitement to even small doses. Large doses may produce CNS stimulation (restlessness, tremor).
Dermatologic - Hypersensitivity: Severe allergic reactions including anaphylaxis, urticaria and other dermal
manifestations.
Other: Suppression of lactation; nasal congestion; decreased sweating. Complete anhidrosis cannot occur because large doses would be required, producing severe side effects from parasympathetic paralysis.

OVERDOSAGE

Symptoms:
GI: Dry mouth; dysphagia; vomiting; nausea; abdominal distention.
CNS: Theoretically, a curare-like action may occur, i.e., neuromuscular blockade leading to muscular weakness and paralysis.
CNS stimulation; delirium; drowsiness; stupor; fever; dizziness; headache; restlessness; seizures; depression; tremor; hallucinations; ataxia; coma; psychotic behavior; other signs of an acute organic psychosis.
Cardiovascular: Circulatory failure; rapid pulse and respiration; tachycardia with weak pulse; hypertension; palpitations.
GU: Urinary urgency with difficulty in micturition.
Ocular: Blurred vision; photophobia; dilated pupils.
Miscellaneous: Leukocytosis, flushed hot dry skin, rash; respiratory failure.

Treatment:
Administer supportive and symptomatic therapy as indicated.
Physostigmine 1 to 3 mg I.V. has been utilized to reverse anticholinergic effects. However, profound bradycardia, asystole and seizures may occur. The role of physostigmine is not clear; its use should be avoided if other therapeutic agents are successful in reversing cardiac dysrhythmias. Neostigmine methylsulfate 0.5 to 2 mg I.V., repeated as needed, may be given. Diazepam or short-acting barbiturates may control excitement. Hemodialysis is ineffective for atropine poisoning. Hyperpyrexia may be treated with physical cooling measures. If photophobia occurs, the patient may be kept in a dark room.

DOSAGE AND ADMINISTRATION

Usual adult dosage:
Antimuscarinic: Intramuscular, intravenous, or subcutaneous, 400 to 600 μg (0.4 to 0.6 mg) every four to six hours.
Arrhythmias: Intravenous, 400 μg (0.4 mg) to 1 mg every one to two hours as needed, up to a maximum of 2 mg.
Gastrointestinal radiography: Intramuscular, 1 mg.
Preanesthesia (antisialagogue): Intramuscular, 200 to 600 μg (0.2 to 0.6 mg) one-half to one hour before surgery.
Cholinergic adjunct (curariform block): Intravenous, 600 μg (0.6 mg) to 1.2 mg administered a few minutes before or concurrently with 500 μg (0.5 mg) to 2 mg of neostigmine methylsulfate, using separate syringes.
Antidote (to cholinesterase inhibitors): Intravenous, 2 to 4 mg initially, then 2 mg repeated every five to ten minutes until muscarinic symptoms disappear or signs of atropine toxicity appear.
Antidote (to muscarine in mushroom poisoning): Intramuscular or intravenous, 1 to 2 mg every hour until respiratory effects subside.
Antidote (to organophosphate pesticides): Intramuscular or intravenous 1 to 2 mg, repeated in twenty to thirty minutes as soon as cyanosis has cleared. Continue dosage until definite improvement occurs and is maintained, sometimes for two days or more.

Usual pediatric dosage
Antimuscarinic: Subcutaneous, 10 μg (0.01 mg) per kg of body weight, not to exceed 400 μg (0.4 mg), or 300 μg (0.3 mg) per square meter of body surface, every four to six hours.
Arrhythmias: Intravenous, 10 to 30 μg (0.01 to 0.03 mg) per kg of body weight.
Preanesthesia (antisialagogue): or
Preanesthesia (antiarrhythmic): Subcutaneous–
Children weighing up to 3 kg: 100 μg (0.1 mg).
Children weighing 7 to 9 kg: 200 μg (0.2 mg).
Children weighing 12 to 16 kg: 300 μg (0.3 mg).
Children weighing 20 to 27 kg: 400 μg (0.4 mg).
Children weighing 32 kg: 500 μg (0.5 mg).
Children weighing 41 kg; 600 μg (0.6 mg).
Antidote (to cholinesterase inhibitors): Intravenous or intramuscular, 1 mg initially, then 0.5 to 1 mg every five to ten minutes until muscarinic symptoms disappear or signs of atropine toxicity appear.

NOTE: Parenteral drug products should be inspected visually for particulate matter and discoloration prior to administration, whenever solution and container permit.

HOW SUPPLIED

Product: 50090-3138

NDC: 50090-3138-0 10 mL in a SYRINGE / 10 in a CARTON